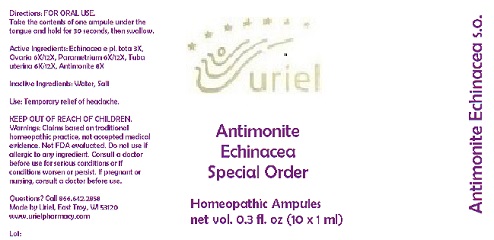 DRUG LABEL: Antimonite Echincea Special Order
NDC: 48951-1241 | Form: LIQUID
Manufacturer: Uriel Pharmacy Inc.
Category: homeopathic | Type: HUMAN OTC DRUG LABEL
Date: 20191127

ACTIVE INGREDIENTS: ECHINACEA, UNSPECIFIED 3 [hp_X]/1 mL; BOS TAURUS OVARY 6 [hp_X]/1 mL; BEEF 6 [hp_X]/1 mL; SUS SCROFA FALLOPIAN TUBE 6 [hp_X]/1 mL; ANTIMONY TRISULFIDE 8 [hp_X]/1 mL
INACTIVE INGREDIENTS: WATER; SODIUM CHLORIDE

Antimonite Echincea Special Order

INDICATIONS AND USAGE

Directions: FOR ORAL USE.

DOSAGE AND ADMINISTRATION

Take the contents of one ampule under the tongue and hold for 30 seconds, then swallow.

ACTIVE INGREDIENT

Active Ingredients: Echinacea e pl. tota 3X, Ovaria 6X/12X, Parametrium 6X/12X, Tuba uterina 6X/12X, Antimonite 8X

Inactive Ingredients: Water, Salt

PURPOSE

Use: Temporary relief of headache.

KEEP OUT OF REACH OF CHILDREN.

WARNINGS

Warnings: Claims based on traditional homeopathic practice, not accepted medical evidence. Not FDA evaluated. Do not use if allergic to any ingredient. Consult a doctor before use for serious conditions or if conditions worsen or persist. If pregnant or nursing, consult a doctor before use.

QUESTIONS

Questions? Call 866.642.2858 Made by Uriel, East Troy, WI 53120 www.urielpharmacy.com